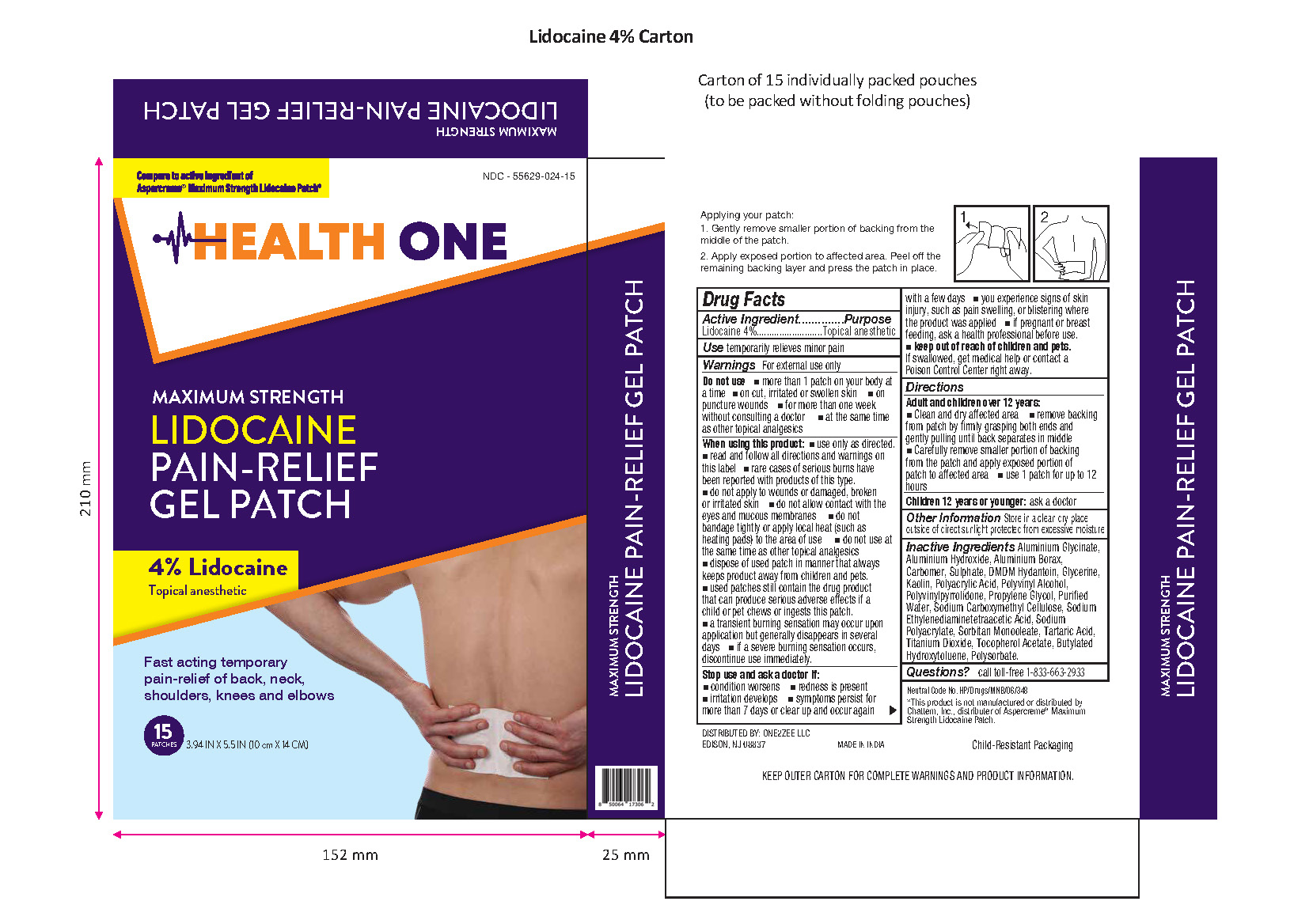 DRUG LABEL: Lidocaine 4% Pain Relief Gel Patch
NDC: 55629-024 | Form: PATCH
Manufacturer: ONE2ZEE LIMITED LIABILITY COMPANY
Category: otc | Type: HUMAN OTC DRUG LABEL
Date: 20250303

ACTIVE INGREDIENTS: LIDOCAINE 40 mg/1 1
INACTIVE INGREDIENTS: ALUMINUM GLYCINATE; ALUMINUM HYDROXIDE; ALUMINUM BORATE; CARBOMER; DMDM HYDANTOIN; ALUMINUM SULFATE; GLYCERIN; KAOLIN; POLYACRYLIC ACID (250000 MW); POLYVINYL ALCOHOL (100000 MW); POVIDONE K27; PROPYLENE GLYCOL; WATER; CARBOXYMETHYLCELLULOSE SODIUM; MAGNESIUM DISODIUM EDTA; SODIUM POLYACRYLATE (2500000 MW); SORBITOL; SORBITOL MONOOLEATE; TARTARIC ACID; TITANIUM DIOXIDE; .ALPHA.-TOCOPHEROL ACETATE; BUTYLATED HYDROXYTOLUENE; POLYSORBATE 20

Lidocaine 4% Pain Relief Gel Patch

Active ingredient

Lidocaine 4%

Purpose

Topical Anesthetic

Use

Temporarily relieves minor pain

Warnings

For external use only

Do not use:

- more than 1 patch on your body at a time
- on cut, irritated or swollen skin
- on puncture wounds
- for more than one week without consulting a doctor
- at the same time as other topical analgesics

When using this product:

• use only as directed.
• read and follow all directions and warnings on this label
• rare cases of serious burns have been reported with products of this type.
• do not apply to wounds or damaged, broken
• eyes and mucous membranes
• do not bandage tightly or apply local heat (such as
• the same time as other topical analgesics
• keeps product away from children and pets. used patches still contain the drug product that can produce serious adverse effects if a child or pet chews or ingests this patch.
• a transient burning sensation may occur upon application but generally disappears in several days
• if a severe burning sensation occurs, discontinue use immediately.
• discontinue use at least 1 hour before a bath or shower.
• do not use immediately after a bath or shower.

Stop use and ask doctor if:

• condition worsen
• redness is present
• irritation develops
• symptoms persist for more than 7 days or clear up and occur again within a few days
• you experience signs of skin injury, such as pain, swelling, or blistering where this product is applied

if pregnant or breast feeding,

ask a health professional before use.

keep out of reach of children and pets

If swallowed, get medical help or contact a Poison Control Center right away.

Directions:

Adult and children over 12years:

- Clean and dry affected area
- remove backing from patch by firmly grasping both ends and
- gently pulling until back separates in middle
- Carefully remove smaller portion of backing from the patch and apply exposed portion of
- patch to affected area
- use 1 patch for up to 12 hours

children 12 years or younger: ask a doctor

Inactive ingredients:

Alpha Tocopherol, Aluminum Sulphate, Borax, Carbomer, Colloidal Silicon Dioxide, DMDM Hydantoin, Glycerin, Kaolin, Polyacrylic Acid, Polyvinyl Alcohol, Polyvinylpyrrolidone , Propylene Glycol, Purified Water, Sodium Carboxymethyl Cellulose, Sodium Ethylenediaminetetraacetic Acid, Sodium Polyacrylate, Sorbitol, Sorbitol Monooleate , Tartaric Acid & Titanium Dioxide, Butylated Hydroxytoluene, Polysorbate

Other Information:

Store at room temperature 20·25'C (68-77'F)

Questions? call toll-free 1-844-912-4012